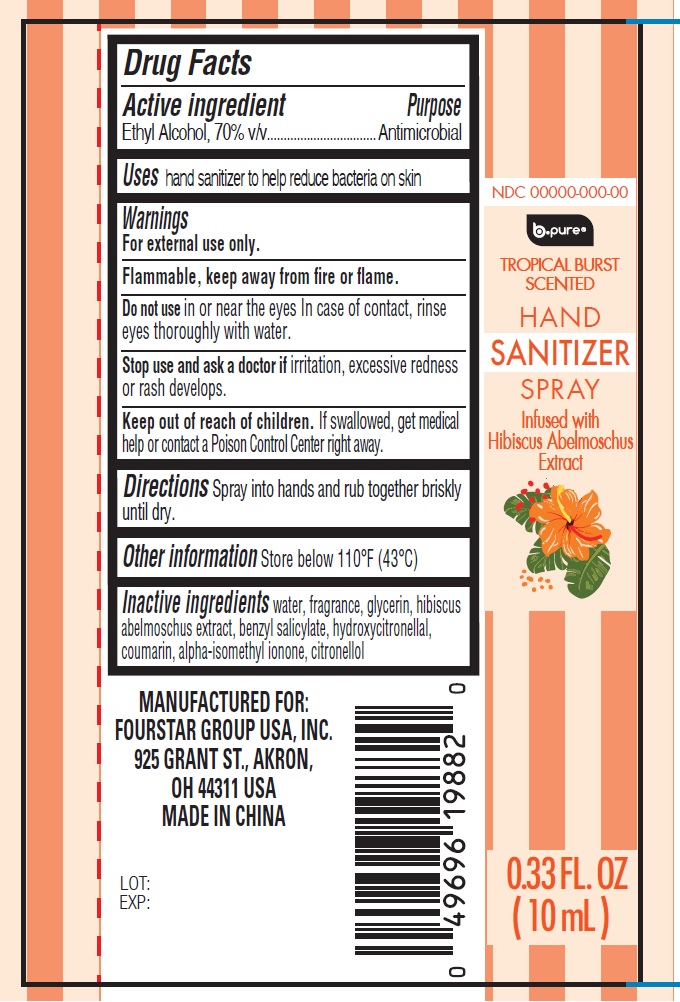 DRUG LABEL: B Pure Hand Sanitizer Tropical Burst Scented
NDC: 80684-194 | Form: LIQUID
Manufacturer: Fourstar Group USA, Inc.
Category: otc | Type: HUMAN OTC DRUG LABEL
Date: 20251210

ACTIVE INGREDIENTS: ALCOHOL 70 mL/100 mL
INACTIVE INGREDIENTS: WATER; GLYCERIN; BENZYL SALICYLATE; HYDROXYCITRONELLAL; COUMARIN; ALPHA-ISOMETHYL IONONE; .BETA.-CITRONELLOL, (R)-

B-Pure Hand Sanitizer Spray Tropical Burst Scented

Active ingredient

Ethyl Alcohol, 70% v/v

Purpose

Antimicrobial

Uses

hand sanitizer to help reduce bacteria on skin

Warnings

For external use only.

Flammable, keep away from fire or flame.

Do not use

in or near the eyes. In case of contact, rinse eyes thoroughly with water.

Stop use and ask a doctor if

irritation, excessive redness or rash develops.

Keep out of reach of children.

If swallowed, get medical help or contact a Poison Control Center right away.

Directions

Spray into hands and rub together briskly until dry.

Other information

Store below 110°F (43°C)

Inactive ingredients

water, fragrance, glycerin, hibiscus abelmoschus extract, benzyl salicylate, hydroxycitronellal, coumarin, alpha-isomethyl ionone, citronellol